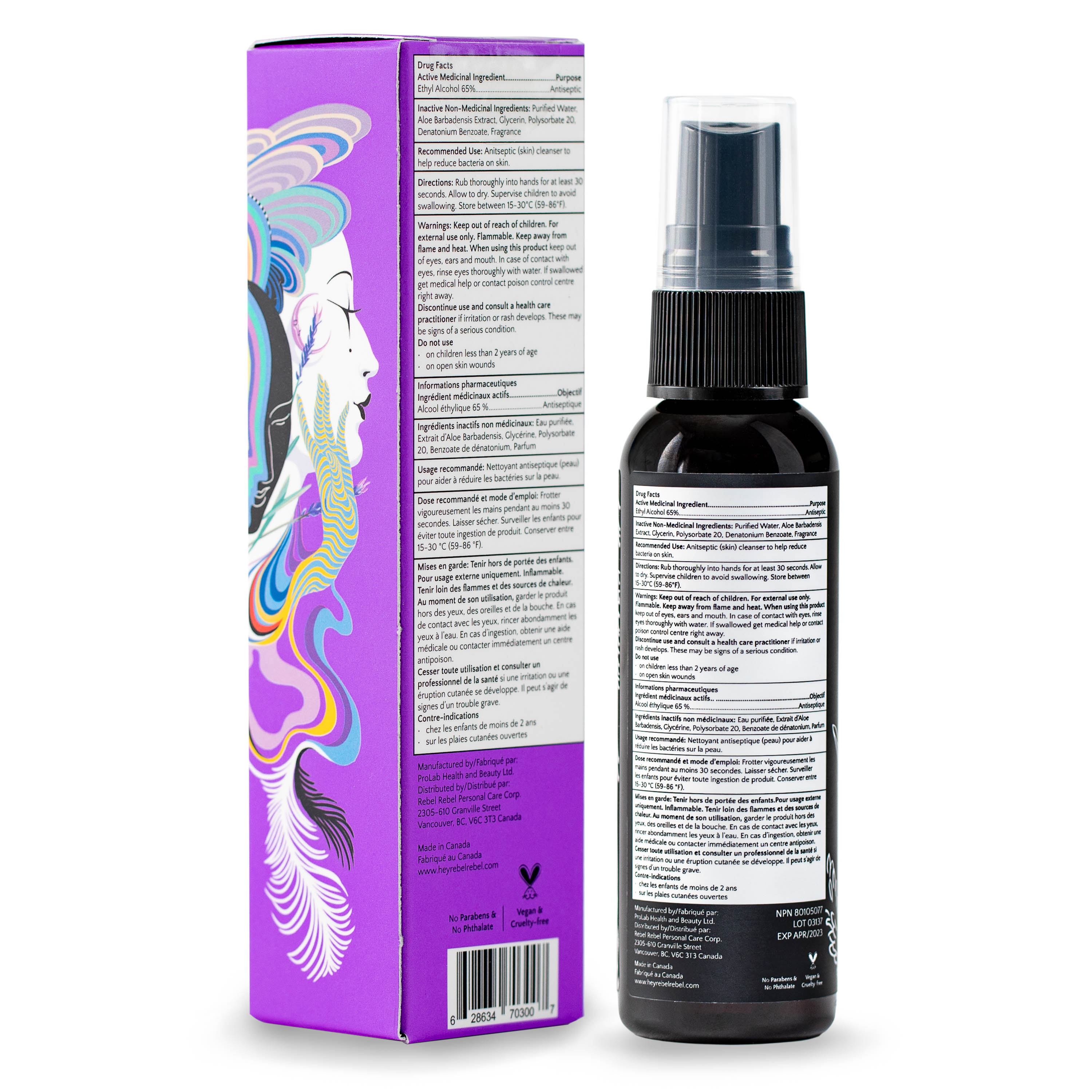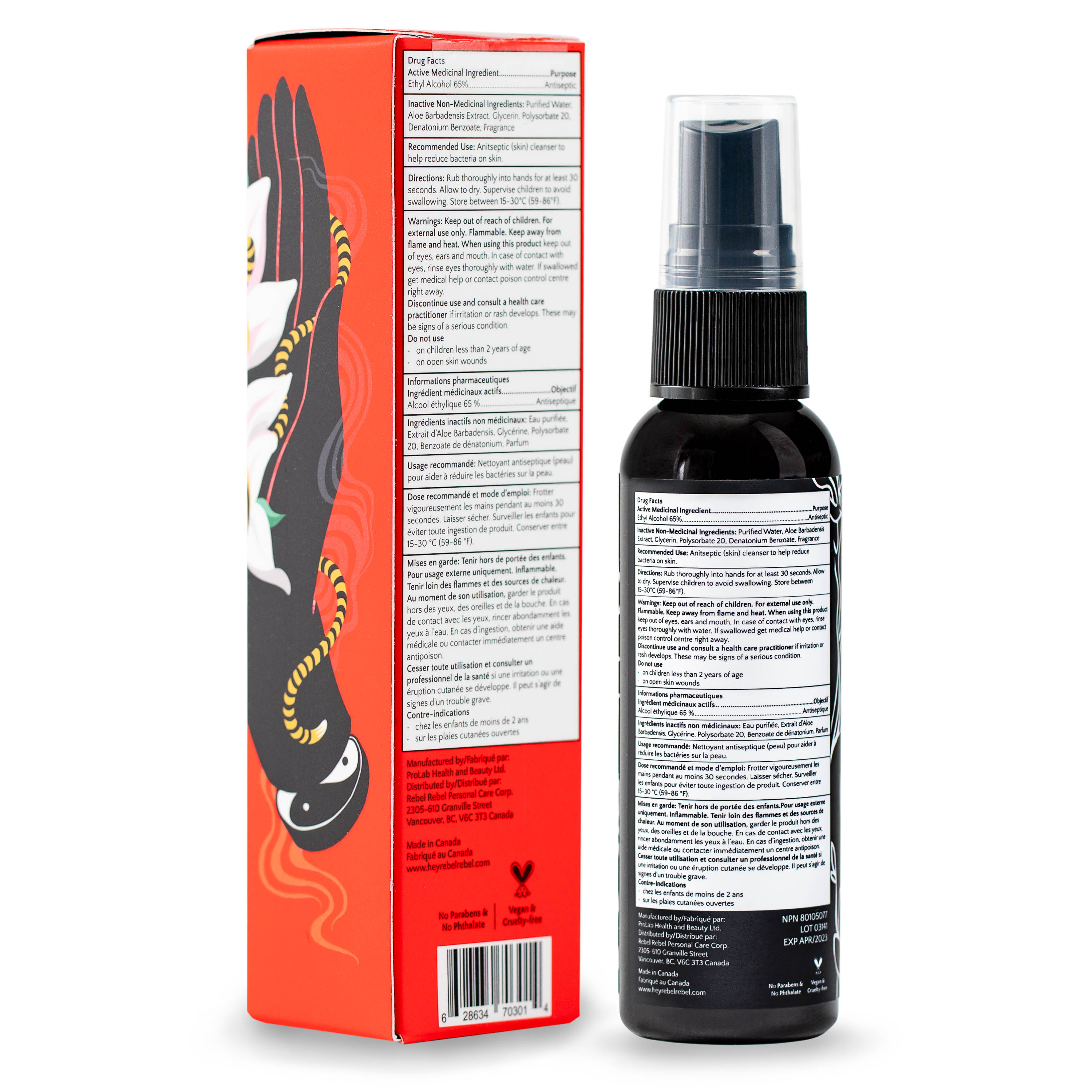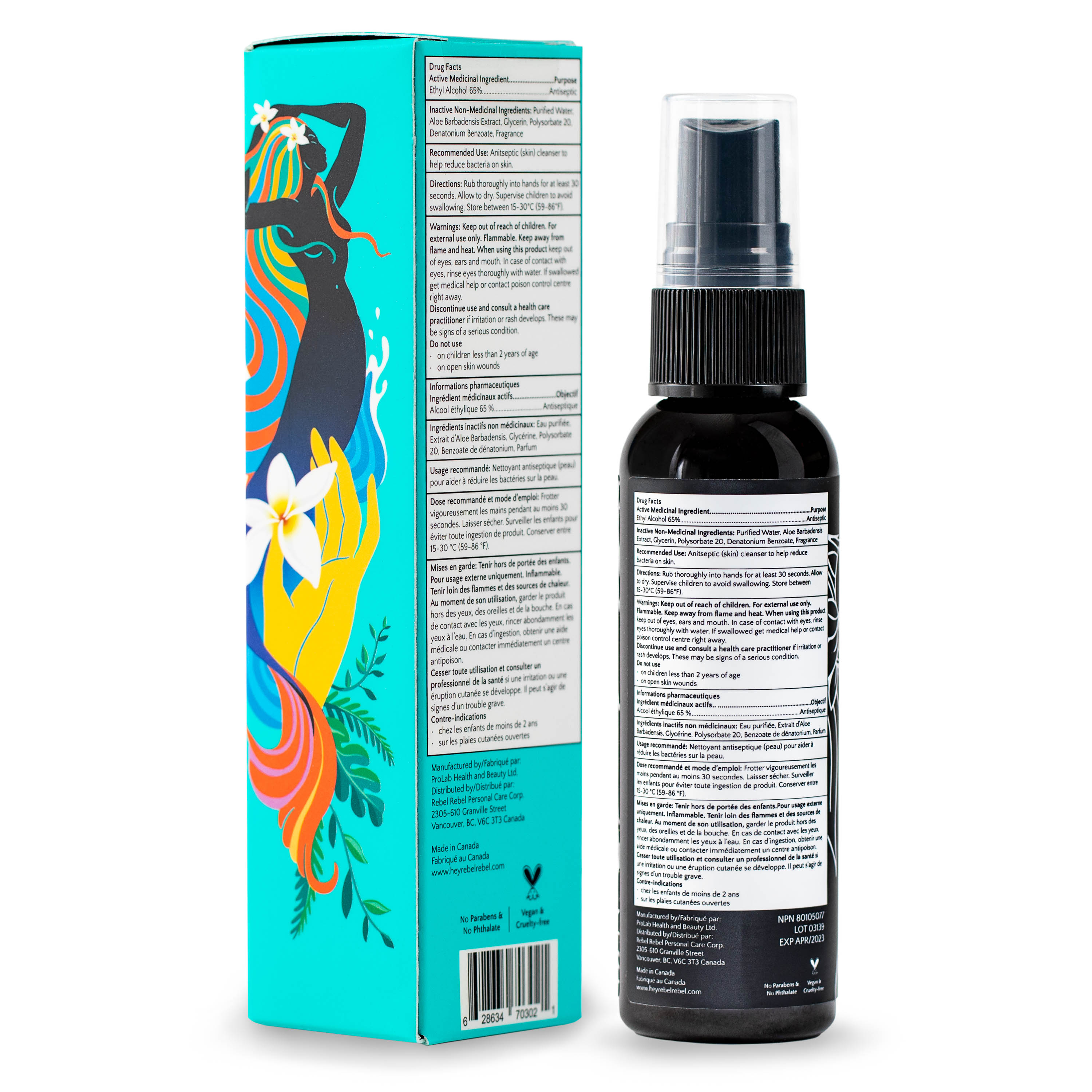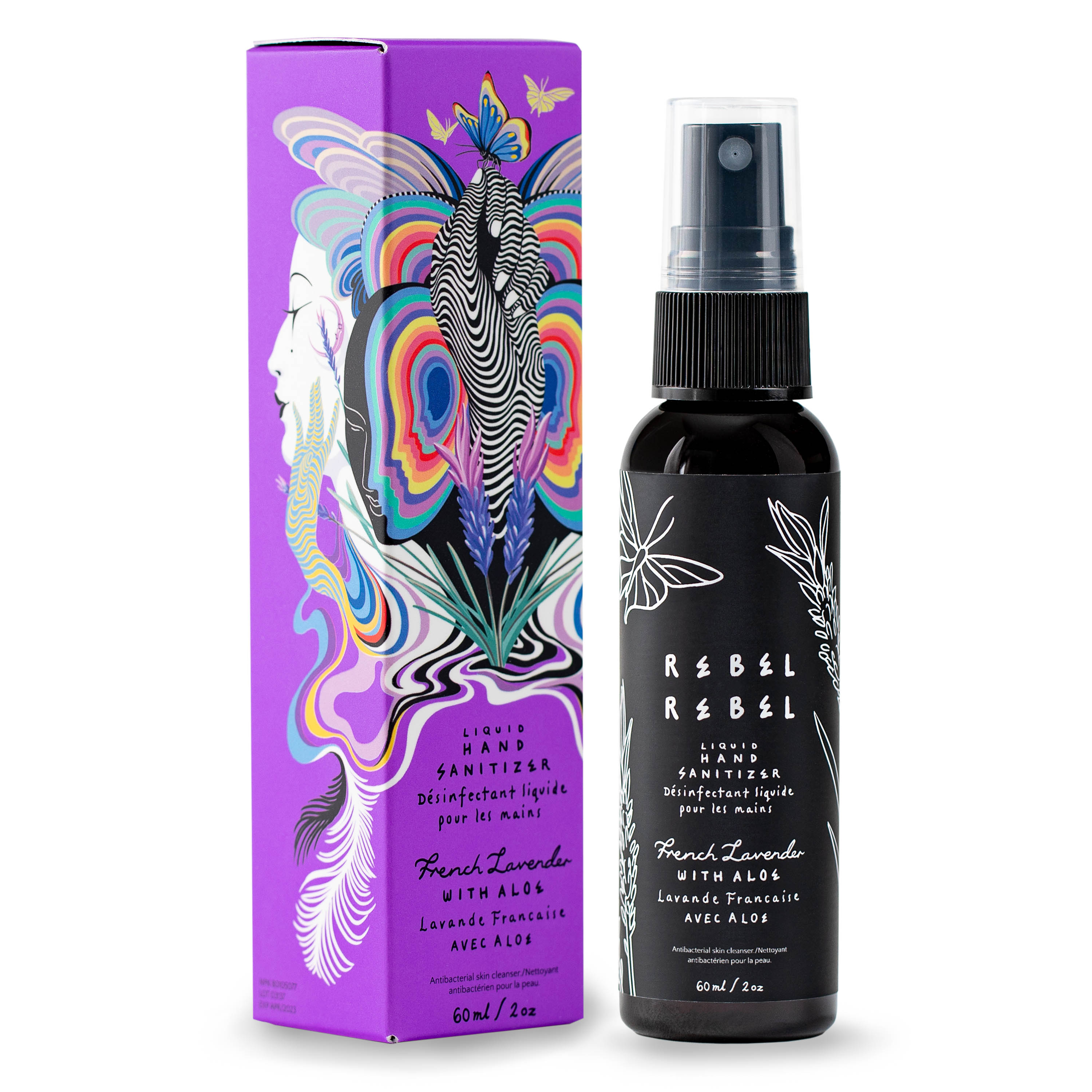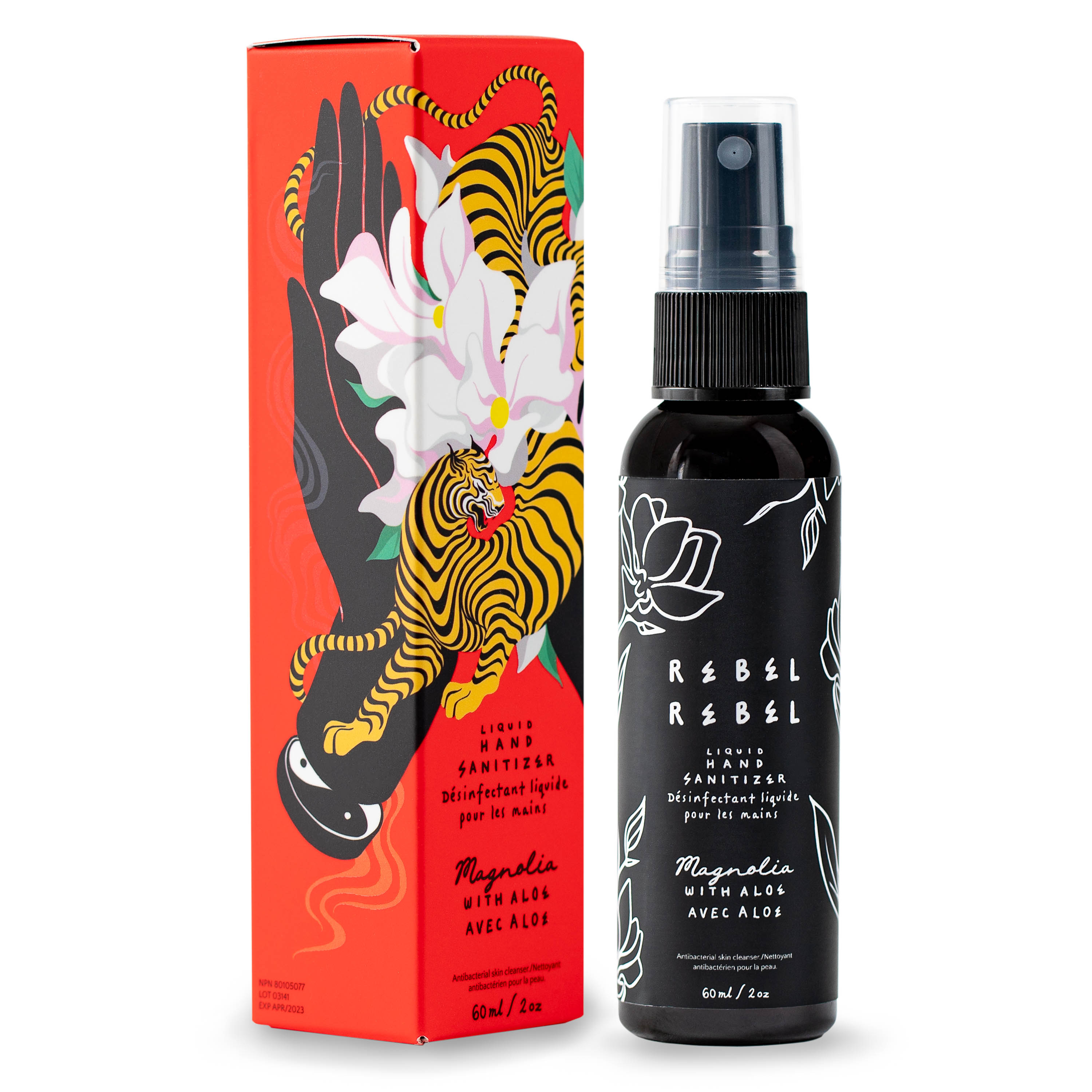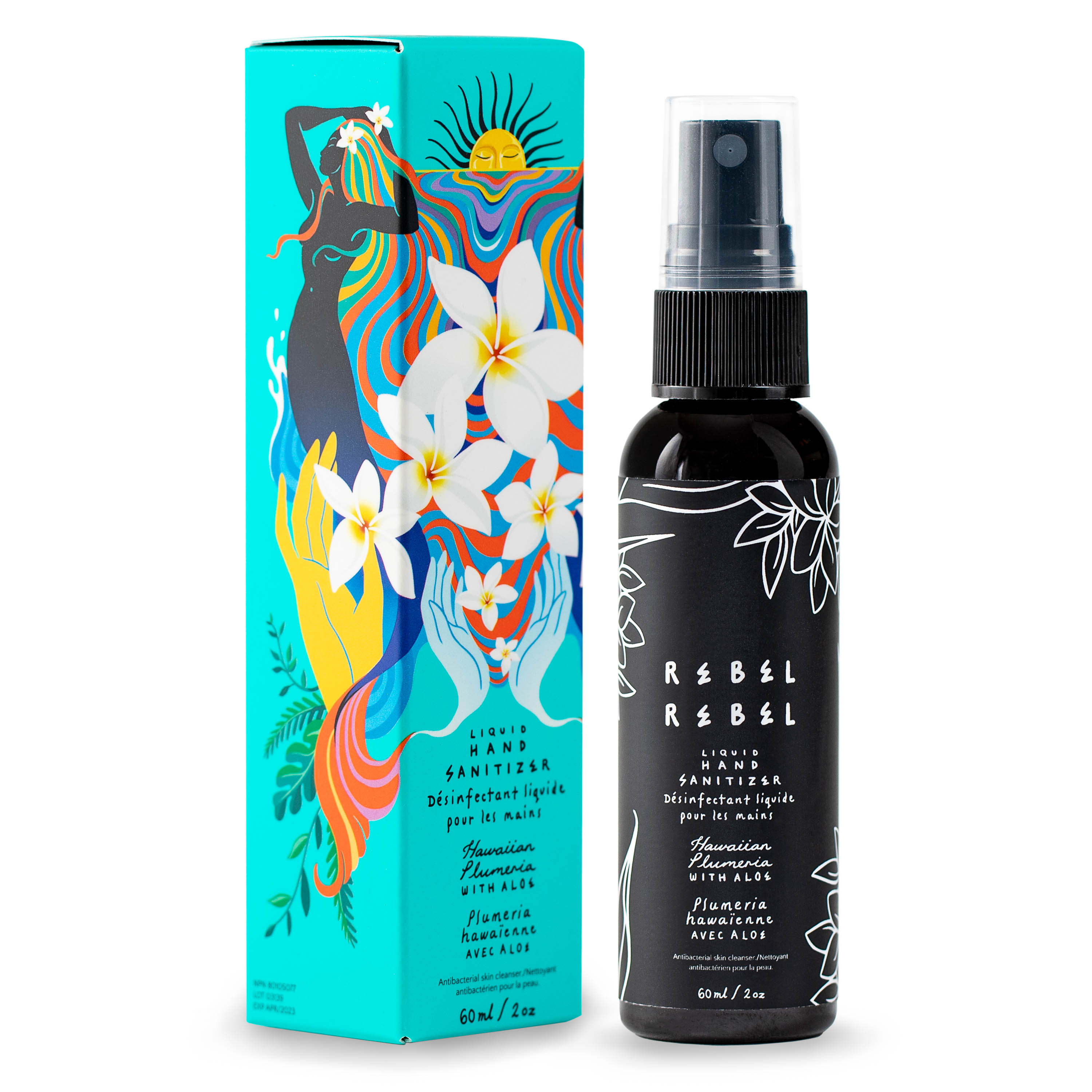 DRUG LABEL: Hand Sanitizer
NDC: 82092-001 | Form: LIQUID
Manufacturer: Rebel Rebel Personal Care Corp.
Category: otc | Type: HUMAN OTC DRUG LABEL
Date: 20230116

ACTIVE INGREDIENTS: ALCOHOL 65 mL/100 mL
INACTIVE INGREDIENTS: POLYSORBATE 20; DENATONIUM BENZOATE; ALOE VERA LEAF; GLYCERIN 1.45 mL/100 mL; WATER

This is a hand sanitizer manufactured according to the Temporary Policy for Preparation of Certain Alcohol-Based Hand Sanitizer Products During the Public Health Emergency (CoViD-19); Guidance for Industry.

The hand sanitizer is manufactured using only the following United States Pharmacopoeia (USP) grade ingredients in the preparation of the product (percentage in final product formulation) consistent with World Health Organization (WHO) recommendations:

1. Alcohol (ethanol) (USP or Food Chemical Codex (FCC) grade) (80%, volume/volume (v/v)) in an aqueous solution denatured according to Alcohol and Tobacco Tax and Trade Bureau regulations in 27 CFR part 20.
2. Glycerol (1.45% v/v).
3. Hydrogen peroxide (0.125% v/v).
4. Sterile distilled water or boiled cold water.

The firm does not add other active or inactive ingredients. Different or additional ingredients may impact the quality and potency of the product.

Active Ingredient(s)

Ethyl Alcohol 65%. Purpose: Antiseptic

Purpose

Antiseptic, Hand Sanitizer

Use

Antiseptic (skin) cleanser to help reduce bacteria on skin.

Warnings

Keep out of reach of children. For external use only. Flammable. Keep away from flame and heat. When using this product keep out of eyes, ears and mouth. In case of contact with eyes, rinse eyes thoroughly with water. If swallowed get medical help or contact poison control centre right away.

Do not use

- in children less than 2 months of age
- on open skin wounds

When using this product keep out of eyes, ears, and mouth. In case of contact with eyes, rinse eyes thoroughly with water.
Stop use and ask a doctor if irritation or rash occurs. These may be signs of a serious condition.
Keep out of reach of children. If swallowed, get medical help or contact a Poison Control Center right away.

Stop use and ask a doctor if irritation or rash occurs. These may be signs of a serious condition.

Keep out of reach of children. If swallowed, get medical help or contact a Poison Control Center right away.

Directions

Rub thoroughly into hands for at least 30 seconds. Allow to dry. Supervise children to avoid swallowing. Store between 15-30°C (59-86°F).

Other information

- Store between 15-30C (59-86F)
- Avoid freezing and excessive heat above 40C (104F)

Inactive ingredients

Non Active Ingredients: Purified Water, Aloe Barbadensis Extract, Glycerin, Polysorbate 20, Denatonium Benzoate, Fragrance.

Changes to:

1. Recommended Use: Antiseptic (skin) cleanser to help reduce bacteria on skin.
2. Direction: Rub thoroughly into hands for at least 30 seconds. Allow to dry. Supervise children to avoid swallowing. Store between 15-30°C (59-86°F).
3. Warnings: Keep out of reach of children. For external use only. Flammable. Keep away from flame and heat. When using this product keep out of eyes, ears and mouth. In case of contact with eyes, rinse eyes thoroughly with water. If swallowed get medical help or contact poison control centre right away.

Package Label - Principal Display Panel

60 mL NDC: 82092-001-01

60 mL NDC: 82092-002-01

60 mL NDC: 82092-003-01